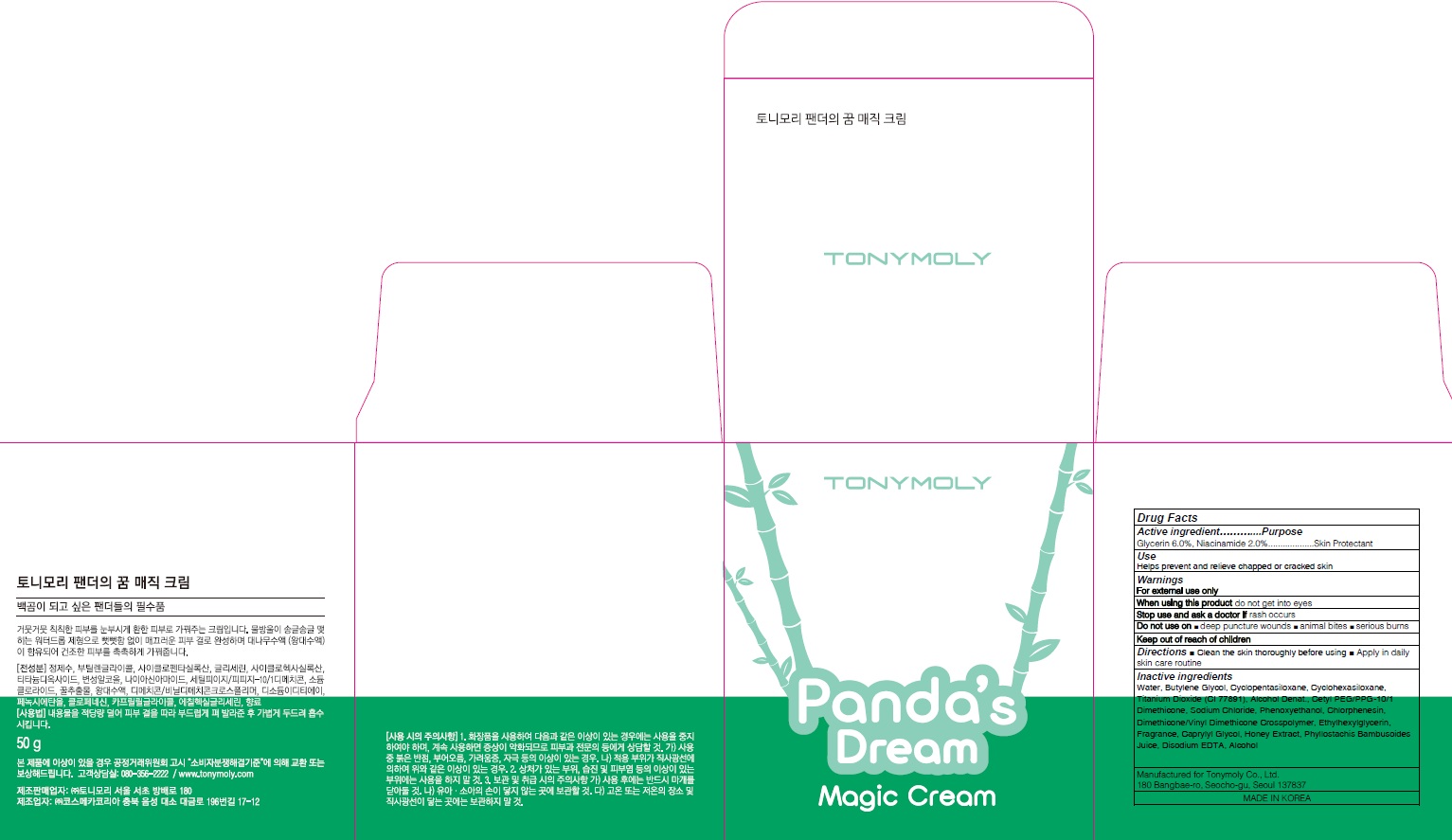 DRUG LABEL: PANDAS DREAM MAGIC
NDC: 59078-312 | Form: CREAM
Manufacturer: TONYMOLY CO.,LTD
Category: otc | Type: HUMAN OTC DRUG LABEL
Date: 20160615

ACTIVE INGREDIENTS: Glycerin 3.0 g/50 g; Niacinamide 1.0 g/50 g
INACTIVE INGREDIENTS: Water; Butylene Glycol

ACTIVE INGREDIENT

Active ingredient: Glycerin 6.0%, Niacinamide 2.0%

INACTIVE INGREDIENT

Inactive Ingredient: Water, Butylene Glycol, Cyclopentasiloxane, Cyclohexasiloxane, Titanium Dioxide (CI 77891), Alcohol Denat., Cetyl PEG/PPG-10/1 Dimethicone, Sodium Chloride, Phenoxyethanol, Chlorphenesin, Dimethicone/Vinyl Dimethicone Crosspolymer, Ethylhexylglycerin, Fragrance, Caprylyl Glycol, Honey Extract, Phyllostachis Bambusoides Juice, Disodium EDTA, Alcohol

PURPOSE

Purpose: Skin Protectant

WARNINGS

Warnings: For external use only. When using this product do not get into eyes. Stop use and ask a doctor if rash occurs. Do not use on - deep puncture wounds - animal bites - serious burns Keep out of reach of children.

KEEP OUT OF REACH OF CHILDREN

Use

Use: Helps prevent and relieve chapped or cracked skin

Directions

Directions: - Clean the skin thoroughly before using - Apply in daily skin care routine